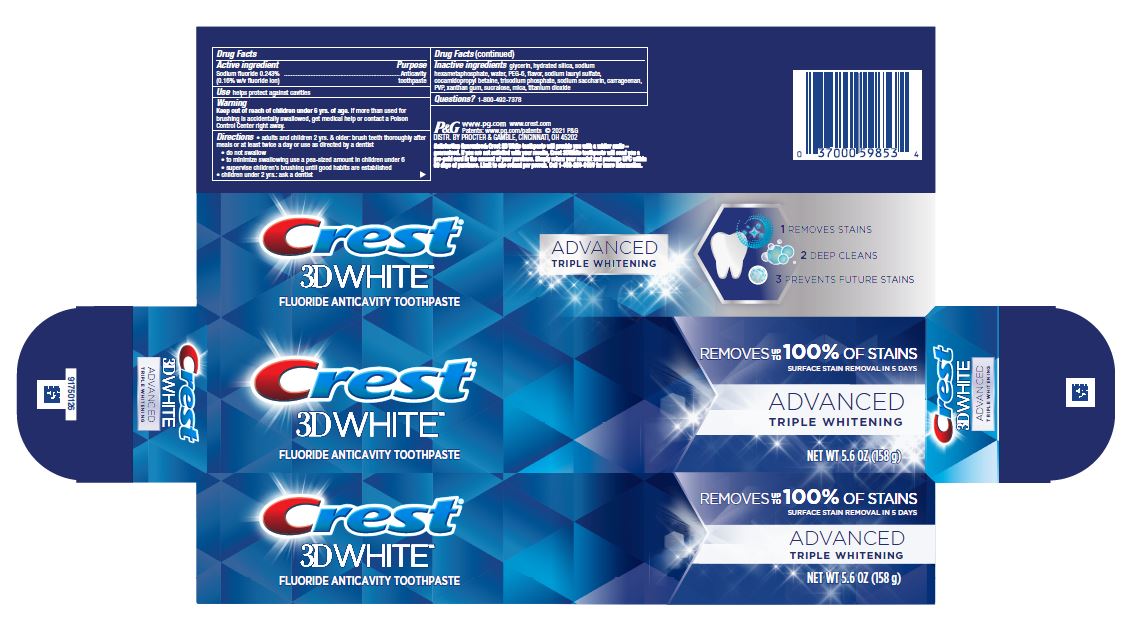 DRUG LABEL: Crest 3D White
NDC: 69423-913 | Form: PASTE, DENTIFRICE
Manufacturer: The Procter & Gamble Manufacturing Company
Category: otc | Type: HUMAN OTC DRUG LABEL
Date: 20250108

ACTIVE INGREDIENTS: SODIUM FLUORIDE 1.6 mg/1 g
INACTIVE INGREDIENTS: GLYCERIN; HYDRATED SILICA; SODIUM POLYMETAPHOSPHATE; WATER; POLYETHYLENE GLYCOL 300; SODIUM PHOSPHATE, TRIBASIC, ANHYDROUS; SODIUM LAURYL SULFATE; CARRAGEENAN; COCAMIDOPROPYL BETAINE; SACCHARIN SODIUM; POVIDONE; XANTHAN GUM; SUCRALOSE; MICA; TITANIUM DIOXIDE

Crest 3D White Advanced Triple Whitening

Drug Facts

Active ingredient

Sodium fluoride 0.243% (0.16% w/v fluoride ion)

Purpose

Anticavity toothpaste

Use

helps protect against cavities

Warning

Keep out of reach of children under 6 yrs. of age. If more than used for brushing is accidentally swallowed, get medical help or contact a Poison Control Center right away.

Directions

- adults and children 2 yrs. & older: brush teeth thoroughly after meals or at least twice a day or use as directed by a dentist
- do not swallow
- to minimize swallowing use a pea-sized amount in children under 6
- supervise children's brushing until good habits are established
- children under 2 yrs.: ask a dentist

Inactive ingredients

glycerin, hydrated silica, sodium hexametaphosphate, water, PEG-6, flavor, sodium lauryl sulfate, cocamidopropyl betaine, trisodium phosphate, sodium saccharin, carrageenan, PVP, xanthan gum, sucralose, mica, titanium dioxide

Questions?

1-800-492-7378

DISTR. BY PROCTER & GAMBLE, CINCINNATI, OH 45202

PRINCIPAL DISPLAY PANEL - 158 g Tube Carton

Crest®
3D WHITE™
FLUORIDE ANTICAVITYTOOTHPASTE

REMOVES UP TO 100% OF STAINS

SURFACE STAIN REMOVAL IN 5 DAYS

ADVANCED

TRIPLE WHITENING

NET WT 5.6 OZ (158 g)